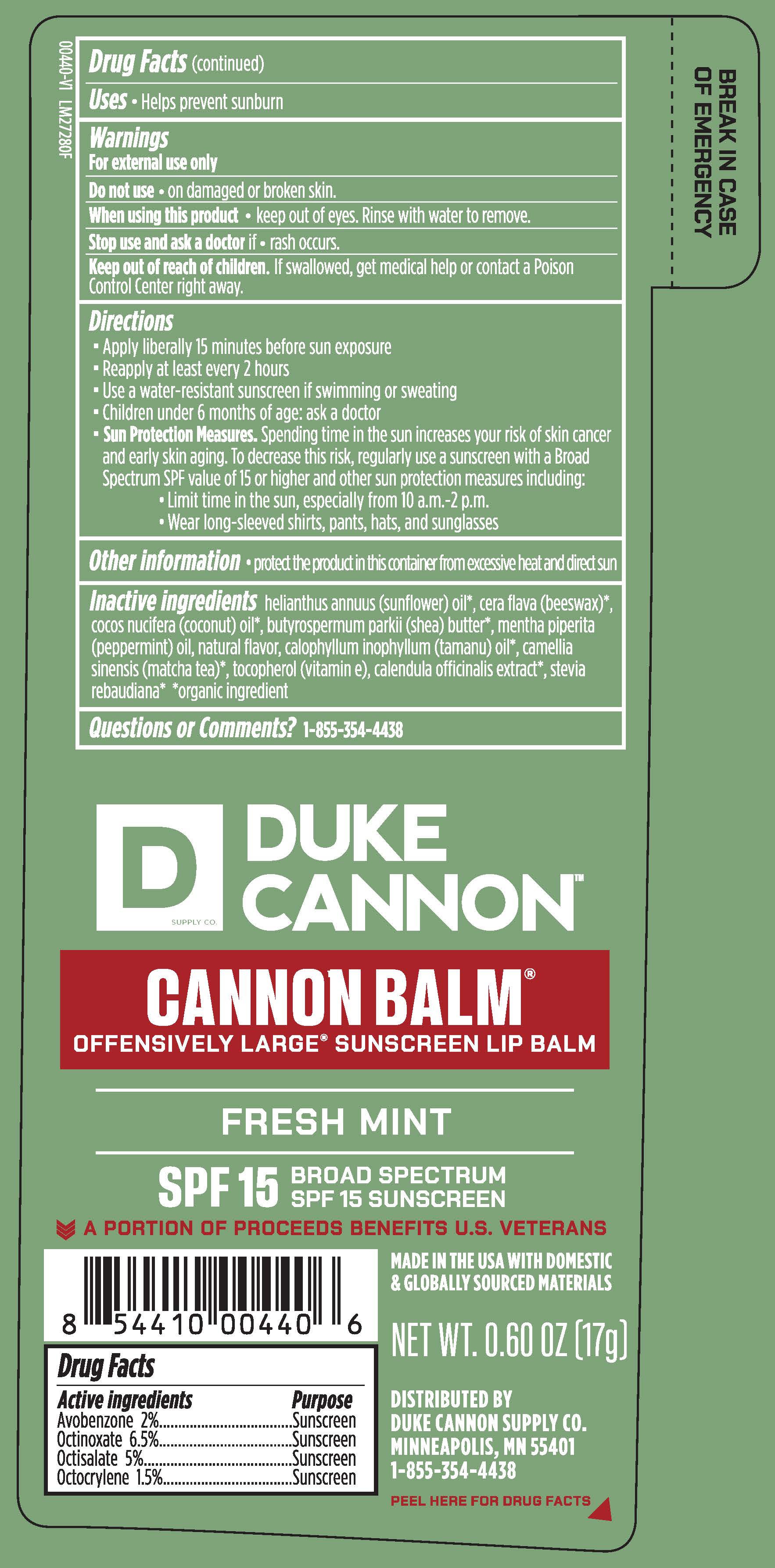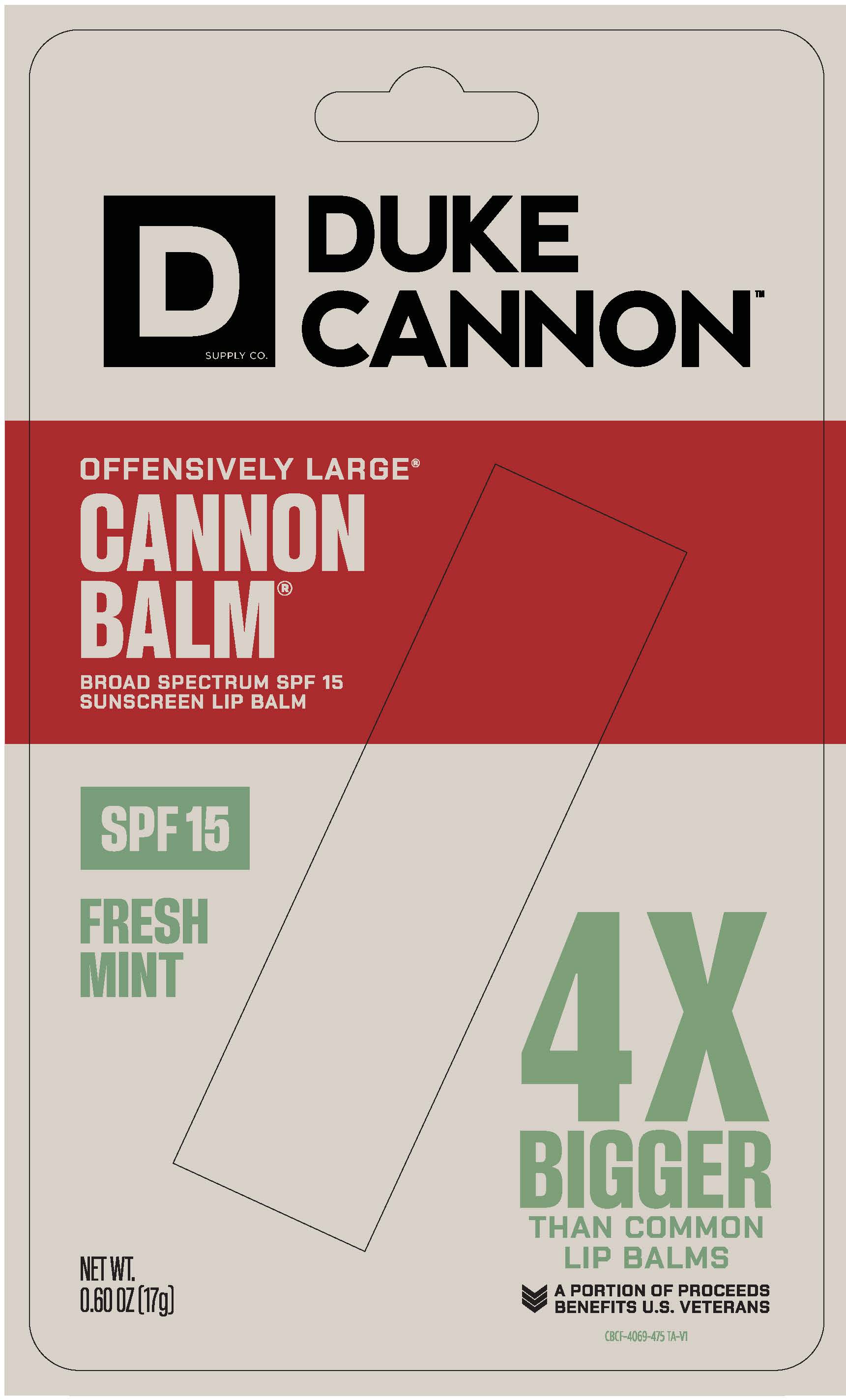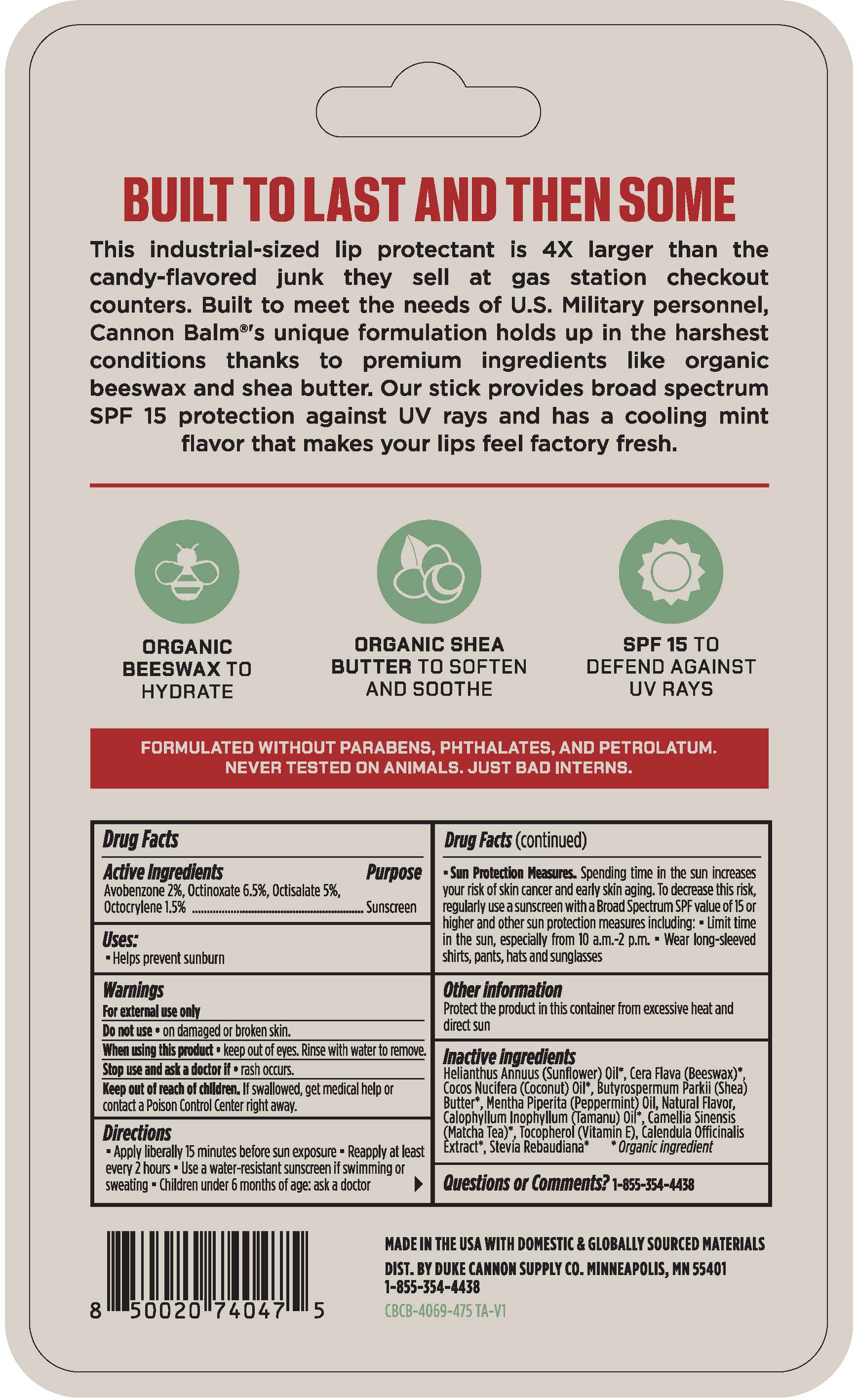 DRUG LABEL: CANNON BALM
NDC: 71782-115 | Form: STICK
Manufacturer: DUKE CANNON SUPPLY CO.
Category: otc | Type: HUMAN OTC DRUG LABEL
Date: 20251203

ACTIVE INGREDIENTS: OCTOCRYLENE 0.255 g/17 g; AVOBENZONE 0.34 g/17 g; OCTINOXATE 1.105 g/17 g; OCTISALATE 0.85 g/17 g
INACTIVE INGREDIENTS: SUNFLOWER OIL; YELLOW WAX; COCONUT OIL; SHEA BUTTER; PEPPERMINT OIL; TAMANU OIL; GREEN TEA LEAF; TOCOPHEROL; CALENDULA OFFICINALIS FLOWER; STEVIA REBAUDIUNA LEAF

90340 Duke Cannon Cannonbalm SPF 15

Drug Facts

Active Ingredients

Avobenzone 2%

Octinoxate 6.5%

Octisalate 5%

Octocrylene 1.5%

Purpose

Sunscreen

Sunscreen

Sunscreen

Sunscreen

INDICATIONS AND USAGE

Uses • H elps prevent sunburn

Warnings

For external use only

Do not use • on damaged or broken skin

When using this product • keep out of eyes. Rinse with water to remove.

Stop use and ask a doctor if • rash occurs

Keep out of reach of children. If swallowed, get medical help or contact a Poison Control Center right away.

Directions

- Apply liberally 15 minutes before sun exposure
- Reapply at least every 2 hours
- Use a water-resistant sunscreen if swimming or sweating
- Children under 6 months of age: ask a doctor
- Sun Protection Measures. Spending time in the sun increases your risk of skin cancer and early skin aging. To decrease this risk, regularly use a sunscreen with a broad spectrum value of 15 or higher and other sun protection measures including:
- limit time in the sun, especially from 10 a.m. - 2 p.m.
- wear long-sleeved shirts, pants, hats and sunglasses

Other Information • protect the product in this container from excessive heat and direct sun

INACTIVE INGREDIENT

Inactive Ingredients helianthus annuus (sunflower) oil*, cera flava (beeswax)*, cocos nucifera (coconut) oil*, butyrospermum parkii (shea) butter*, mentha piperita (peppermint) oil, natural flavor, calophyllum inophyllum (tamanu) oil*, camellia sinensis (matcha tea)*, tocopherol (vitamin e), calendula officinalis extract*, stevia rebaudiana* *organic ingredient

Questions or Comments? 1-855-354-4438

Tube Label Text

DUKE

CANNON

SUPPLY CO.

CANNON BALM®

OFFENSIVELY LARGE® SUNSCREEN LIP BALM

FRESH MINT

SPF 15 BROAD SPECTRUM

SPF 15 SUNSCREEN

A PORTION OF PROCEEDS BENEFITS U.S. VETERANS

MADE IN USA WITH DOMESTIC

& GLOBALLY SOURCED MATERIALS

NET WT. 0.60 OZ (17g)

DISTRIBUTED BY

DUKE CANNON SUPPLY CO.

MINNEAPOLIS, MN 55401

1-855-354-4438

PEEL HERE FOR DRUG FACTS

Blister Carton Text

DUKE

CANNONTM

SUPPLY CO

OFFENSIVELY LARGE®

CANNON

BALM®

BROAD SPECTRUM SPF 15

SUNSCREEN LIP BALM

SPF 15

FRESH

MINT

4x

BIGGER

THAN COMMON

LIP BALMS

A PORTION OF PROCEEDS

BENEFITS U.S. VETERANS

NET WT 0.60 OZ (17G)

BUILT TO LAST AND THEN SOME

This industrial-sized lip protectant is 4X larger than the

candy-flavored junk they sell at gas station checkout

counters. Built to meet the needs of U.S. Military personnel,

Cannon Balm®'s unique formulation holds up in the harshest

conditions thanks to premium ingredients like organic

beeswax and shea butter. Our stick provides broad spectrum

SPF 15 protection against UV rays and has a cooling mint

flavor that makes your lips feel factory fresh.

ORGANIC BEESWAX TO HYDRATE

ORGANIC SHEA BUTTER TO SOFTEN AND SOOTHE

SPF 15 TO DEFEND AGAINST UV RAYS

FORMULATED WITHOUT PARABENS, PHTHALATES, AND PETROLATUM.

NEVER TESTED ON ANIMALS. JUST BAD INTERNS

MADE IN THE USA WITH DOMESTIC & GLOBALLY SOURCED MATERIALS.

DIST. BY DUKE CANNON SUPPLY CO. MINNEAPOLIS, MN 55401

1-855-354-4438

RECENT MAJOR CHANGES

Uses section: added a bullet

Directions section: moved the "children under six" bullet point before the "sun protection measures" bullet.